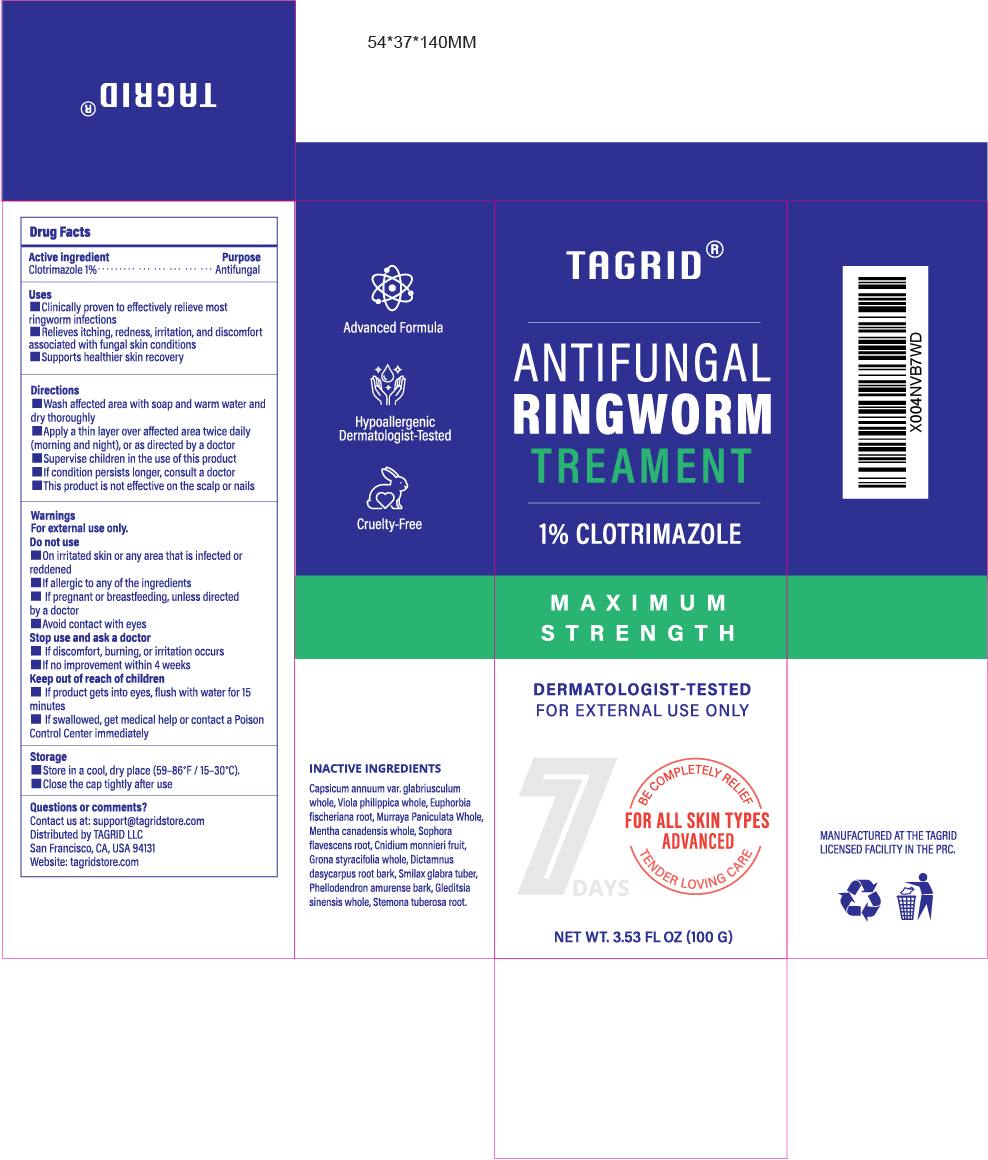 DRUG LABEL: Tagrid Antifungal Ringworm Treatment 1% CLOTRIMAZOLE
NDC: 85384-0006 | Form: CREAM
Manufacturer: TAGRID LLC
Category: otc | Type: HUMAN OTC DRUG LABEL
Date: 20250520

ACTIVE INGREDIENTS: CLOTRIMAZOLE 1 g/100 g
INACTIVE INGREDIENTS: CAPSICUM ANNUUM VAR. GLABRIUSCULUM WHOLE; VIOLA PHILIPPICA WHOLE; EUPHORBIA FISCHERIANA ROOT; MURRAYA PANICULATA WHOLE; STEMONA TUBEROSA ROOT; MENTHA CANADENSIS WHOLE; SOPHORA FLAVESCENS ROOT; CNIDIUM MONNIERI FRUIT; GRONA STYRACIFOLIA WHOLE; DICTAMNUS DASYCARPUS ROOT BARK; SMILAX GLABRA TUBER; PHELLODENDRON AMURENSE BARK; GLEDITSIA SINENSIS WHOLE

Tagrid Antifungal Ringworm Treatment 1% CLOTRIMAZOLE

ACTIVE INGREDIENT

Clotrimazole 1%

PURPOSE

Antifungal

Uses:

1. Clinically proven to effectively relieve most ringworm infections.
2. [Relieves itching, redness, irritation, and discomfort associated with fungal skin conditions.
3. Supports healthier
4. skin recovery

WARNINGS

For external use only.

Do not use:

1. On irritated skin or any area that is infected or reddened
2. If allergic to any of the ingredients.
3. If pregnant or breastfeeding, unless directed by a doctor.
4. Avoid contact with eyes

Stop use and ask a doctor if:
discomfort, burning, or irritation occurs lf no improvement within 4 weeks

Do not use:
If pregnant or breastfeeding, unless directed by a doctor.

Keep out of reach of children.

- If product gets intoeyes,flush with water for 15 minutes.
- If swallowed, get medical help or contact a Poison Control Center immediately

Directions:

1. Wash affected area with soap and warm water and dry thoroughly
2. Apply a thin layer over affected area twice daily (morning and night),or as directed by a doctor
3. Supervise children in the use of this product
4. If condition persists longer, consult a doctor
5. This product is not effective on the scalp or nails.

OTHER SAFETY INFORMATION

1. Store in a cool,dry place (59-86°F/15-30°C)
2. Close the cap tightly after use

Questions or comments?

- Contact us at: support@tagridstore.com
- Distributed by TAGRID LLC
- San Francisco, CA, USA 94131
- Website: tagridstore.com

INACTIVE INGREDIENT

1. Capsicum annuum var. glabriusculum Whole
2. Viola philippica Whole
3. Euphorbia fischeriana Root
4. Murraya exotica Whole
5. Mentha canadensis Whole
6. Sophora flavescens Root
7. Cnidium monnieri Fruit
8. Grona styracifolia Whole
9. Dictamnus dasycarpus Root Bark
10. Smilax glabra Tuber
11. Phellodendron amurense Bark
12. Gleditsia sinensis Whole
13. Stemona tuberosa Root

Initial submission. No prior changes.